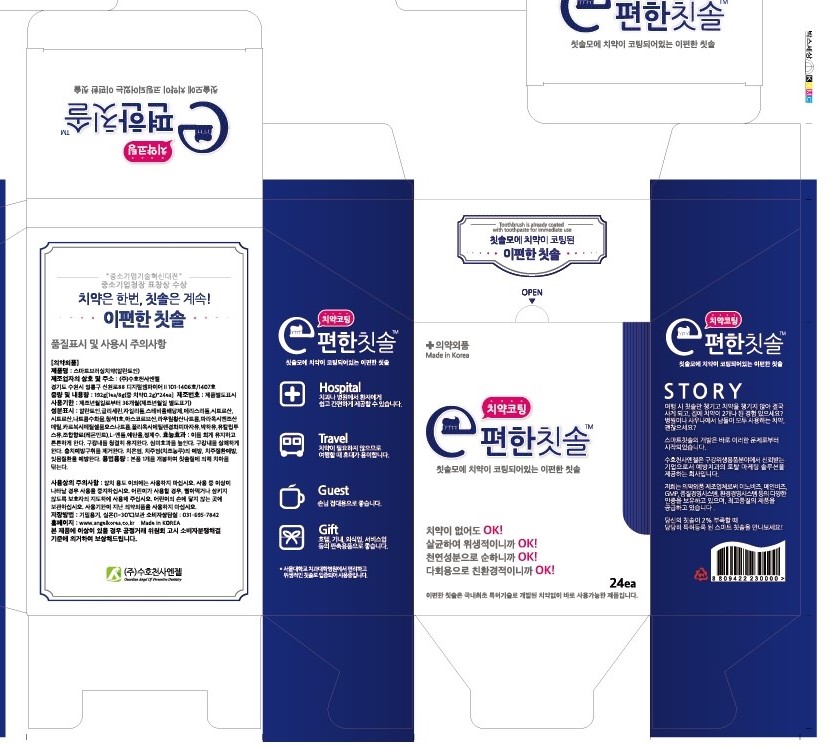 DRUG LABEL: Smart Brushing Tooth
NDC: 69086-0001 | Form: PASTE, DENTIFRICE
Manufacturer: Guardian Angel Co.,Ltd.
Category: otc | Type: HUMAN OTC DRUG LABEL
Date: 20190604

ACTIVE INGREDIENTS: ALLANTOIN 0.1 mg/100 g
INACTIVE INGREDIENTS: XYLITOL; WATER

ACTIVE INGREDIENT

ALLATOIN

PURPOSE

For dental care

Keep out of reach of children

INDICATIONS AND USAGE

Open one of these products and brush your teeth by brushing your teeth.

WARNINGS

Storage method

1. Keep it at room temperature in a classified container.

2. Cover and store at room temperature.

3. Store in a not moisture and cool place.

4. Air may come out during use of this product, but there is no problem with its weight.

Usage Precautions

1. Be careful not to swallow. Rinse mouth thoroughly after use

2. If the use of toothpaste causes abnormalities such as gums or mouth injury, discontinue use and consult a doctor or dentist.

3. For children under 6 years of age, use a small amount of toothpaste as small as pea per use, and use under the guidance of a guardian to avoid sucking or swallowing.

4. If a child under 6 years old swallows large amount, consult with a doctor or dentist immediately.

5. Keep out of the reach of children under 6 years of age.

INACTIVE INGREDIENT

GLYCERIN

XYLITOL

STEVIOL GLYCOSIDE

ERYTHRITOL

CITRIC ACID

SODIUM CITRATE

BLUE NO1 (BRILLIANT BLUE) 1/250

ASCORBIC ACID

SODIUM LAURYL SULFATE

METHYL P-HYDROXYBENZOATE

CARBOXYMETHYL CELLULOSE

POE(60) HYDROGENATED CASTOR OIL

PEPPERMINT

EUCALYPTUS OIL

LEMON OIL

L-MENTHOL

ETHANOL

WATER

DOSAGE AND ADMINISTRATION

For dental use only